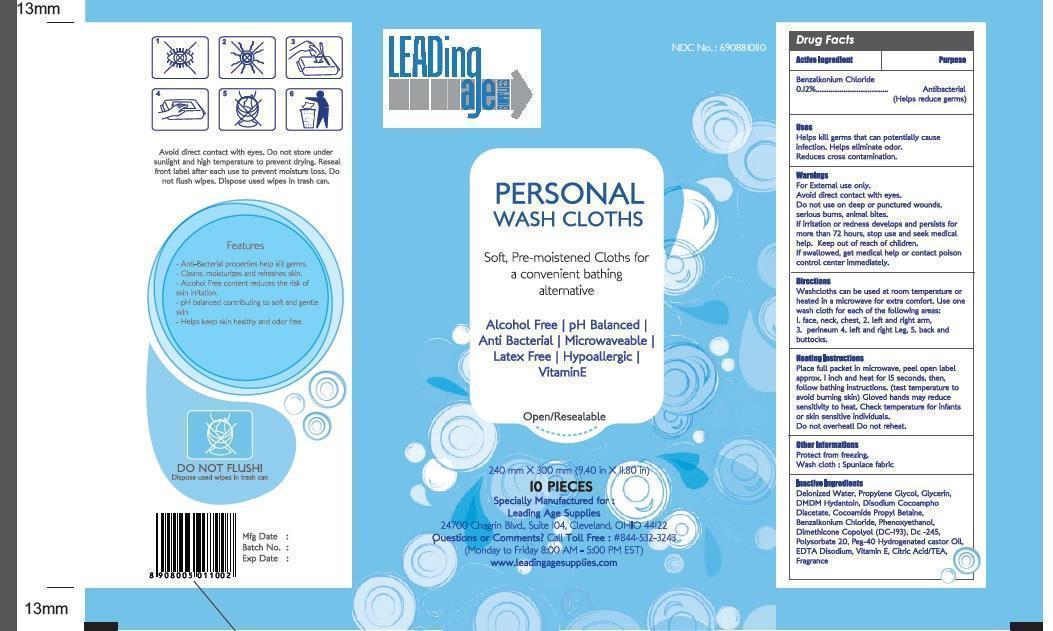 DRUG LABEL: Personal Wash Cloths
NDC: 69089-101 | Form: CLOTH
Manufacturer: Ginni Filaments Limited
Category: otc | Type: HUMAN OTC DRUG LABEL
Date: 20141123

ACTIVE INGREDIENTS: BENZALKONIUM CHLORIDE 0.0155 g/1 1
INACTIVE INGREDIENTS: WATER; PROPYLENE GLYCOL; GLYCERIN; DMDM HYDANTOIN; DISODIUM COCOAMPHODIACETATE; COCAMIDOPROPYL BETAINE; PHENOXYETHANOL; DIMETHICONE; CYCLOMETHICONE 5; POLYSORBATE 20; POLYOXYL 40 HYDROGENATED CASTOR OIL; EDETATE DISODIUM; .ALPHA.-TOCOPHEROL; CITRIC ACID MONOHYDRATE; TROLAMINE

Personal Wash Cloths

Active ingredient

Benzalkonium Chloride 0.12%

Purpose

Antibacterial

(Helps reduce germs)

Keep out of reach of children. If swallowed, get medical help or contact a Poison Control Center right away.

Uses

Helps kill germs that can potentially cause infection.
Helps eliminate odor.

Reduces cross contamination

Warnings

For external use only

Avoid direct contact with eyes.
Do not use on deep or punctured wounds, serious burns, animal bites

If irritation or redness develops, and persists for more than 72 hours, stop use and seek medical help.

Directions

Washcloths can be used at room temperature or heated in a microwave for extra comfort.

Use one wash cloth for each of the following areas

1. Face, Neck, Chest 2. Left and right arm, 3. Perineum, 4.Left and Right leg, 5.Back and Buttocks

Heating instructions

Place full packet in microwave, peel open label approx. 1 inch and heat for 15 seconds, then, follow bathing instructions.(test temperature to avoid burning skin) gloved hands may reduce sensitivity to heat. Check temperature for infants or skin sensitive individuals

Do not overheat! Do not reheat.

Other informations

Protect from freezing

Wash cloth: Spun lace fabric

INACTIVE INGREDIENTS

Deionized water,Propylene Glycol, Glycerin,DMDM Hydantoin, Disodium cocoampho Diacetate, Cocoamide Propyl Betaine, Phenoxyethanol, Dimethicon copolyol(DC-193), DC-245, Polysorbate 20, Peg -40 -Hydrogenated Castor Oil, EDTA Disodium, Vitamin E, Citric Acid/TEA, Fragrance